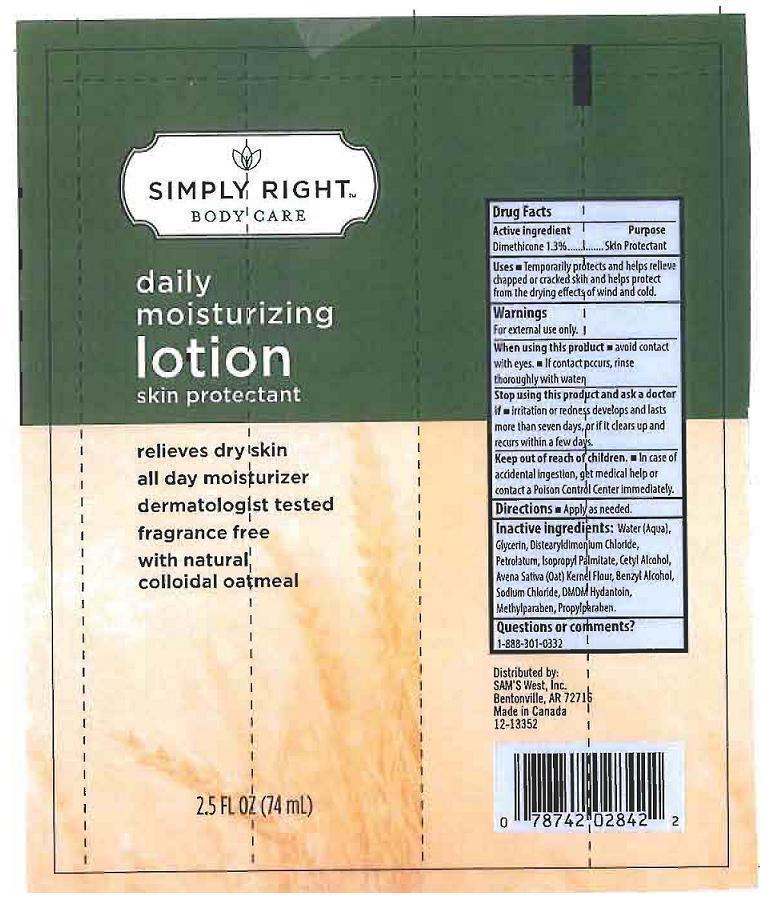 DRUG LABEL: SIMPLY RIGHT BODY CARE
NDC: 68196-324 | Form: LOTION
Manufacturer: SAM'S WEST INC.
Category: otc | Type: HUMAN OTC DRUG LABEL
Date: 20130206

ACTIVE INGREDIENTS: DIMETHICONE 13 mg/1 mL
INACTIVE INGREDIENTS: WATER; GLYCERIN; DISTEARYLDIMONIUM CHLORIDE; PETROLATUM; ISOPROPYL PALMITATE; CETYL ALCOHOL; OATMEAL; BENZYL ALCOHOL; SODIUM CHLORIDE; DMDM HYDANTOIN; METHYLPARABEN; PROPYLPARABEN

DRUG FACTS

ACTIVE INGREDIENT

DIMETHICONE 1.3%

PURPOSE

SKIN PROTECTANT

USES

TEMPORARILY PROTECTS AND HELPS RELIEVE CHAPPED OR CRACKED SKIN AND HELPS PROTECT FROM THE DRYING EFFECTS OF WIND AND COLD.

WARNINGS

FOR EXTERNAL USE ONLY.

WHEN USING THIS PRODUCT

AVOID CONTACT WITH EYES. IF CONTACT OCCURS, RINSE THOROUGHLY WITH WATER.

STOP USING THIS PRODUCT AND ASK A DOCTOR IF

IRRITATION OR REDNESS DEVELOPS AN DLASTS MORE THAN SEVEN DAYS, OR IF IT CLEARS UP AND RECURS WITHIN A FEW DAYS.

KEEP OUT OF REACH OF CHILDREN.

IN CASE OF ACCIDENTAL INGESTION, GET MEDICAL HELP OR CONTACT A POISON CONTROL CENTER IMMEDIATELY.

DIRECTIONS

APPLY AS NEEDED.

INACTIVE INGREDIENTS:

WATER (AQUA), GLYCERIN, DISTEARYLDIMONIUM CHLORIDE, PETROLATUM, ISOPROPYL PALMITATE, CETYL ALCOHOL, AVENA SATIVA (OAT) KERNEL FLOUR, BENZYL ALCOHOL, SODIUM CHLORIDE, DMDM HYDANTOIN, METHYLPARABEN, PROPYLPARABEN.

QUESTIONS OR COMMENTS?

1-888-301-0332